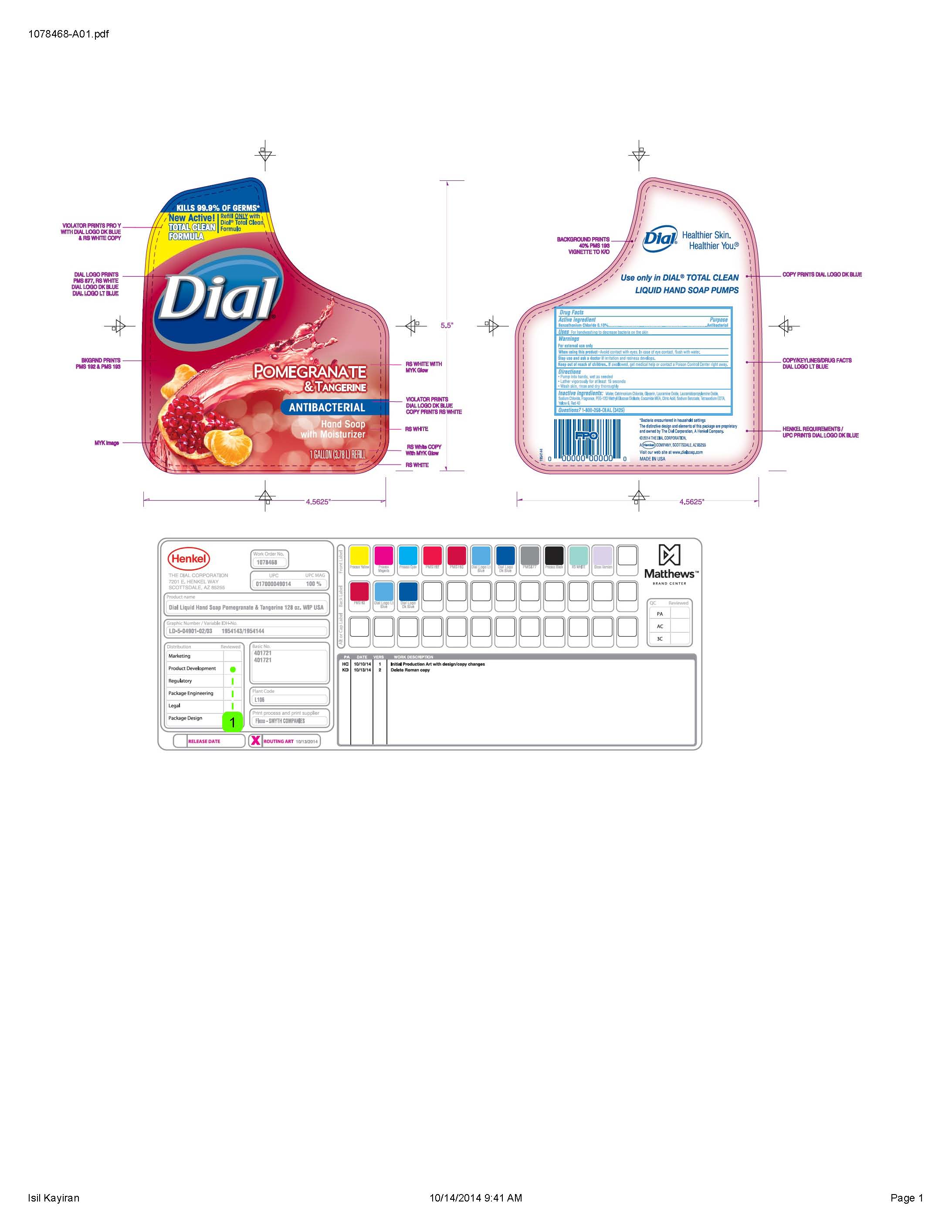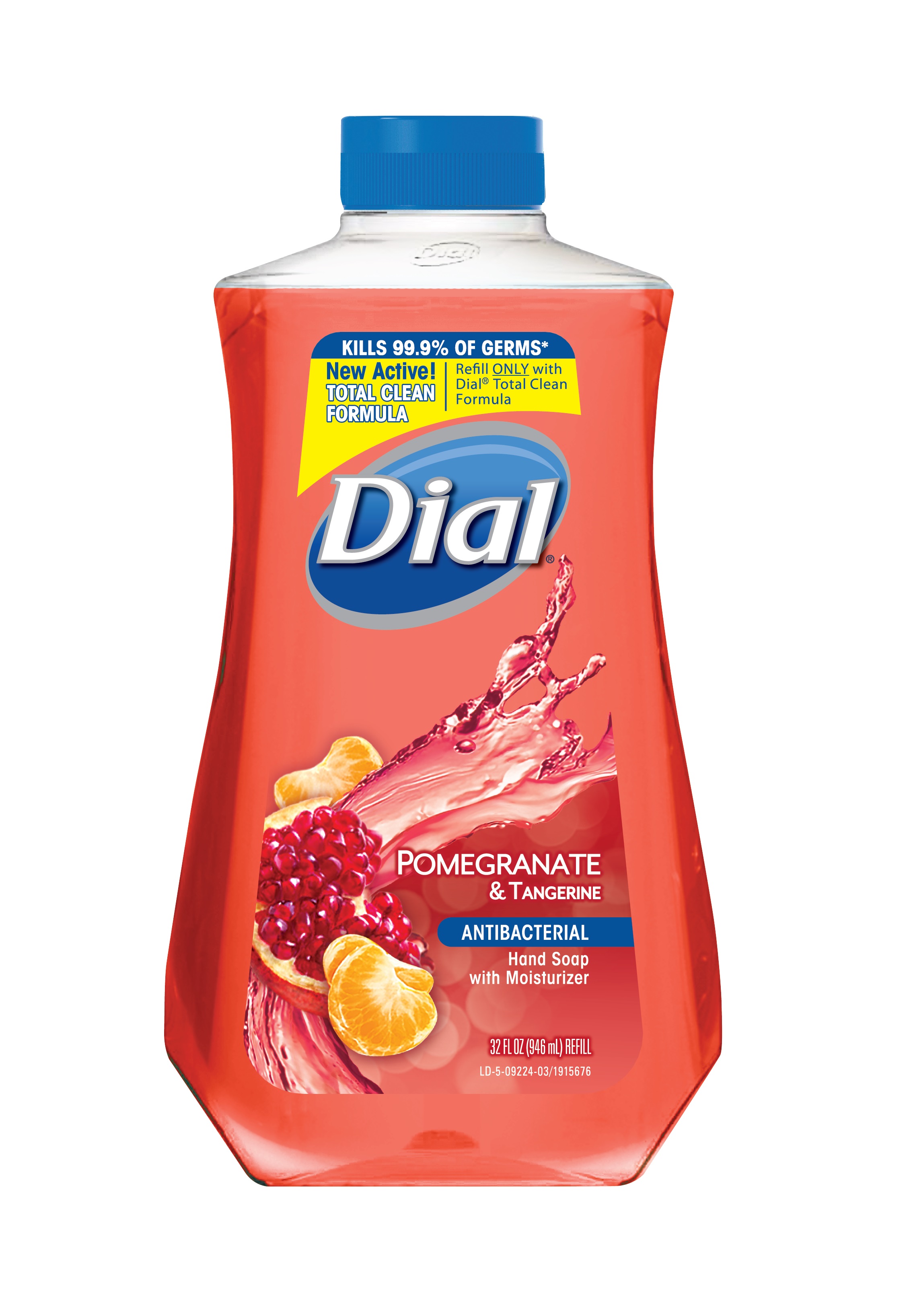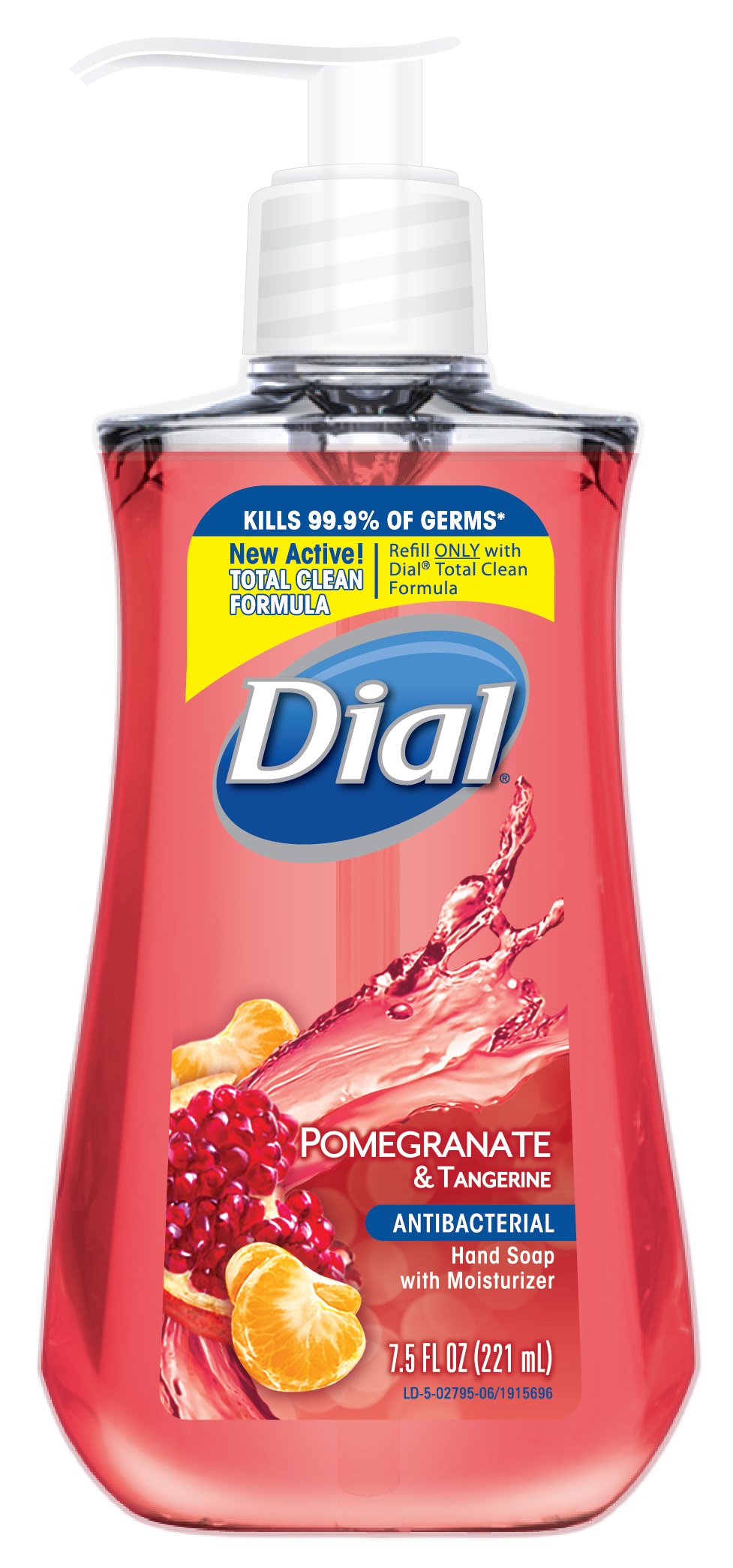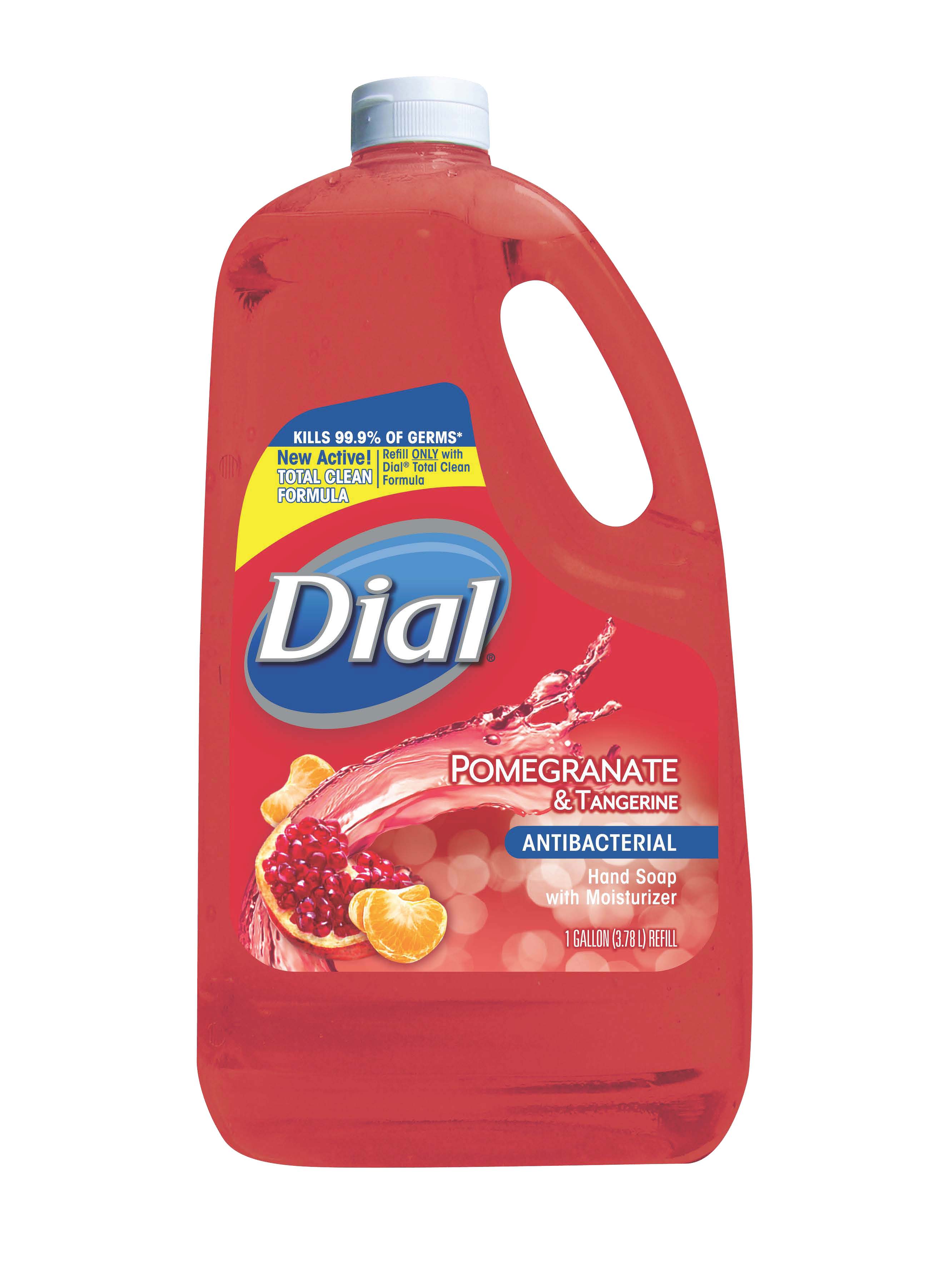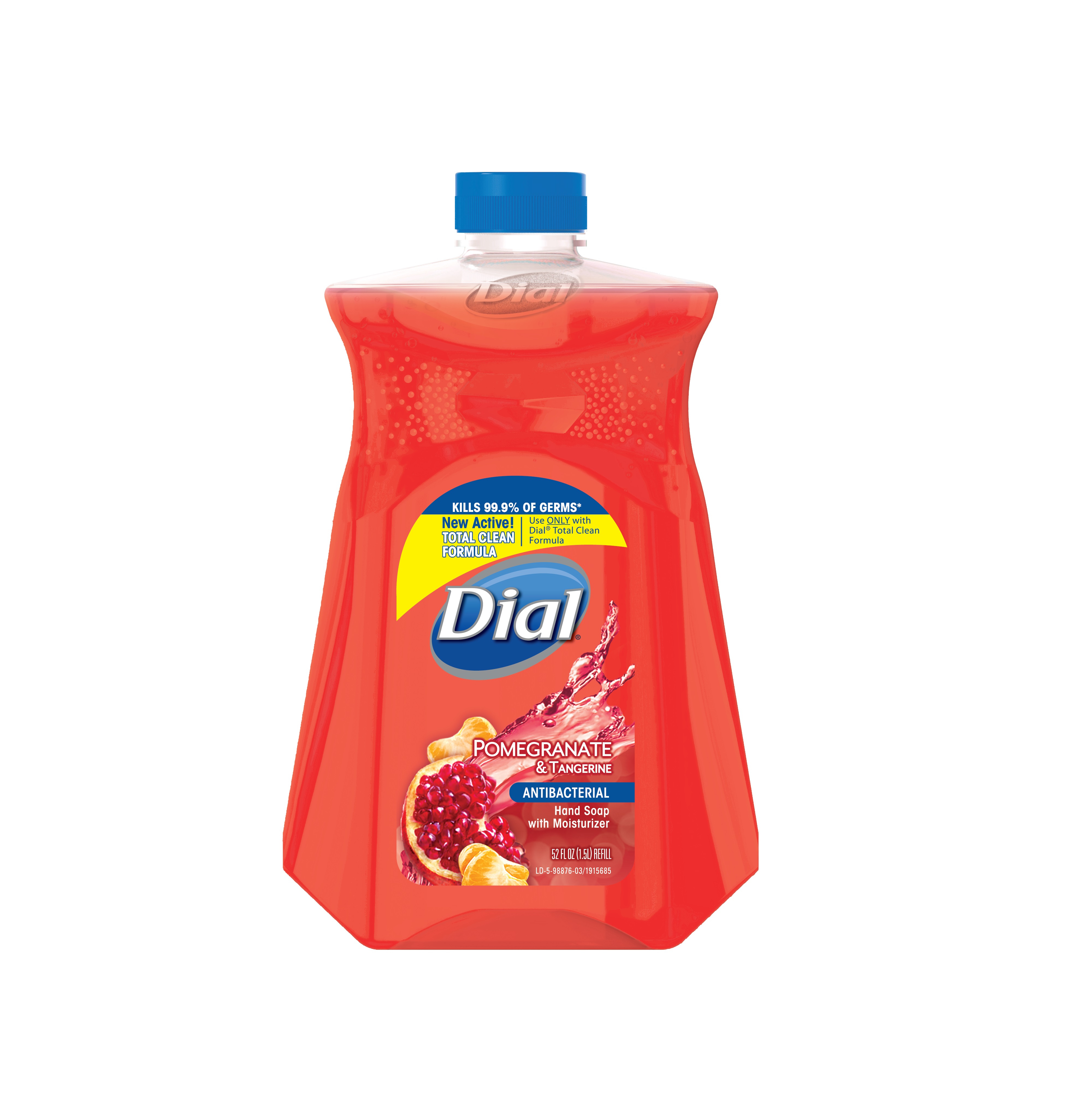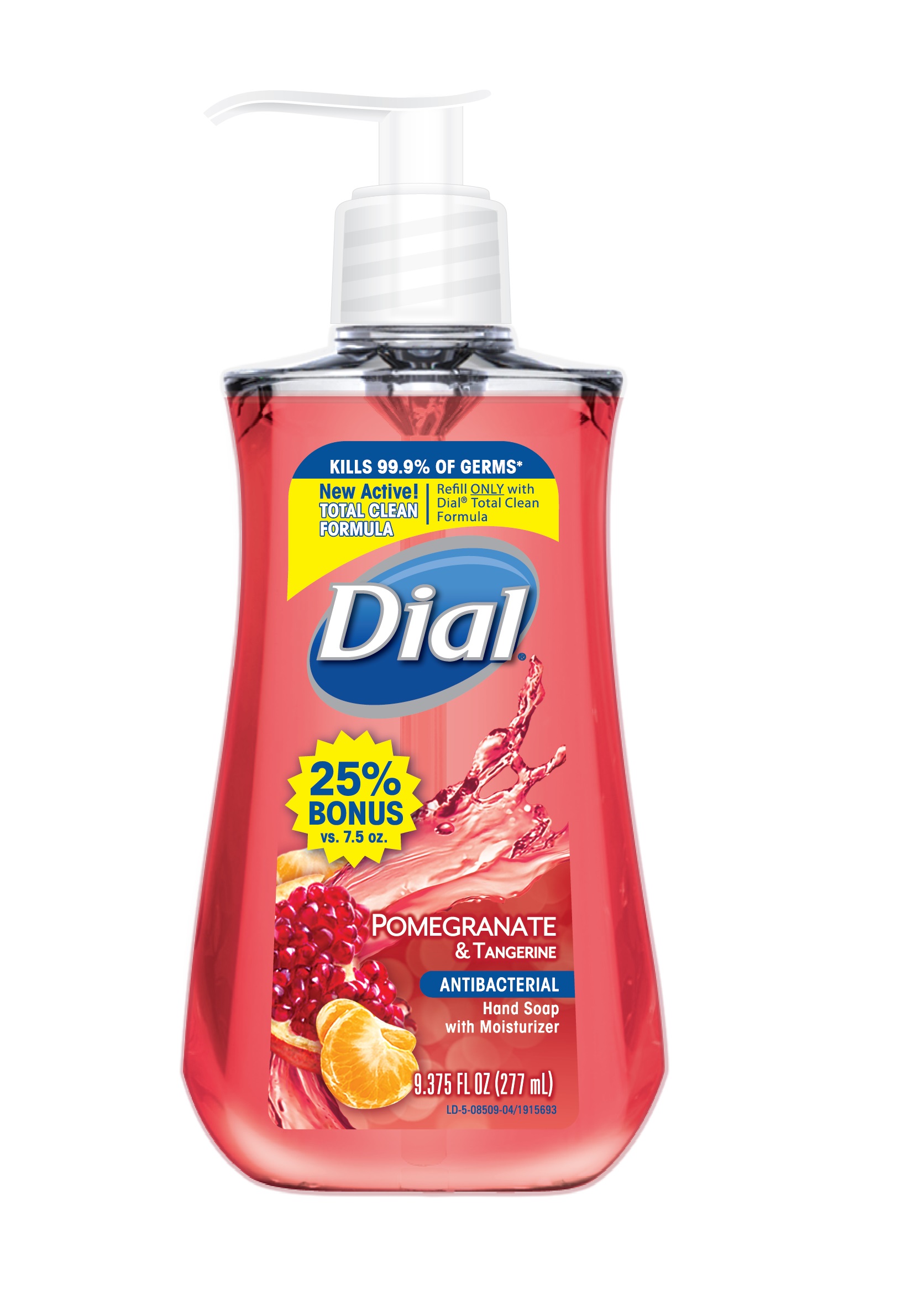 DRUG LABEL: Dial Antibacterial Hand Wash
NDC: 54340-244 | Form: SOLUTION
Manufacturer: The Dial Corporation, a Henkel Company
Category: otc | Type: HUMAN OTC DRUG LABEL
Date: 20141216

ACTIVE INGREDIENTS: Benzethonium Chloride .1 g/100 mL
INACTIVE INGREDIENTS: COCO MONOETHANOLAMIDE; Lauramine Oxide; GLYCERIN; CETRIMONIUM CHLORIDE; D&C RED NO. 33; Sodium Chloride; Lauramidopropylamine Oxide; PEG-120 Methyl Glucose Dioleate; EDETATE SODIUM; Sodium Benzoate; CITRIC ACID MONOHYDRATE; FD&C YELLOW NO. 6; FD&C RED NO. 40

Dial Pomegranate and Tangerine Antibacterial Hand Soap with Moisturizer

Drug Facts

ACTIVE INGREDIENT

Benzethonium Chloride 0.10%

PURPOSE

Antibacterial

PURPOSE

Uses - For handwashing to decrease bacteria on the skin

WARNINGS

For external use only

When using this product - Avoid contact with eyes. In case of eye contact, flush with water.

Stop use and ask doctor if irritation and redness develops

Keep out of reach of children. If swallowed, get medical help or contact a Poison Control Center right away

INSTRUCTIONS FOR USE

pump into hands, wet as needed

later vigorously for at least 15 seconds

wash skin, rinse thoroughly and dry

INACTIVE INGREDIENT

Inactive Ingredients: Water, Centrimonium Chloride, Glycerin, Lauramine Oxide, Lauramidopropylamine Oxide, Sodium Chloride, Fragrance, PEG-120 Methyl Glucose Dioleate, Cocamide MEA, Citric Acid, Sodium Benzoate, Tetrasodium EDTA, Yellow 6, Red 40

* Encountered in household settings

Questions? 1-800-258-DIAL (3425)

Visit our website at www.dialsoap.com MADE IN USA

©2014 & Distributed by THE DIAL CORPORATION
a Henkel COMPANY SCOTTSDALE, AZ 85255

The distinctive design and elements of this package are propriatary and
owned by The Dial Corporation, A Henkel Company

DOSAGE AND ADMINISTRATION

Topical liquid

INDICATIONS AND USAGE

For handwashing to decrease bacteria on skin

Front label

Kills 99.9% of Germs*

New Active!
TOTAL CLEAN FORMULA

Refill ONLY with Dial© Total Clean Formula

DIAL Pomegranite and Tangerine Hand Soap with Moisturizer
Antibacterial
7.5 FL OZ (221 mL)